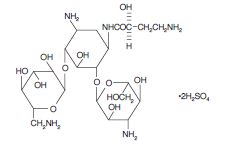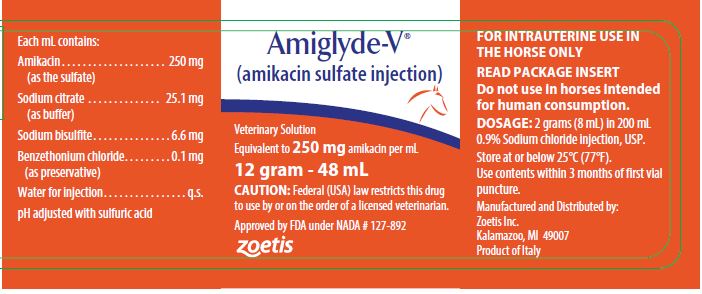 DRUG LABEL: Amiglyde-V
NDC: 54771-2332 | Form: INJECTION
Manufacturer: Zoetis Inc.
Category: animal | Type: PRESCRIPTION ANIMAL DRUG LABEL
Date: 20200319

ACTIVE INGREDIENTS: AMIKACIN SULFATE 250 mg/1 mL

Amiglyde-V® (amikacin sulfate injection)
Veterinary Solution
Equivalent to 250 mg amikacin per mL

Caution

Federal (USA) law restricts this drug to use by or on the order of a licensed veterinarian.

DESCRIPTION

Amikacin sulfate is a semi-synthetic aminoglycoside
antibiotic derived from kanamycin. It is C22H43N5O13•2H2SO4, D-streptamine, 0-3-amino-3-
deoxy-α-D-glucopyranosyl-(1→6)-0-[6-amino-6- deoxy-α-D-glucopyranosyl-(1→4)]-N1-(4-amino-2-
hydroxy-1-oxobutyl)-2-deoxy-, (S)-, sulfate (1:2) (salt).

The dosage form supplied is a sterile, colorless solution.
The solution contains, in addition to amikacin sulfate, USP, 2.5% sodium citrate, USP with pH
adjusted to 4.5 with sulfuric acid and 0.66% sodium bisulfite added. The multi-dose 12 gram–48 mL
vial contains 0.01% benzethonium chloride, USP as a preservative.

ACTION

Antibacterial Activity
The effectiveness of AMIGLYDE-V (amikacin sulfate injection) in infections caused by Escherichia
coli, Pseudomonas sp and Klebsiella sp has been demonstrated clinically in the horse. In addition,
the following microorganisms have been shown to be susceptible to amikacin in vitro1, although the
clinical significance of this action has not been demonstrated in animals:
• Enterobacter sp
• Proteus mirabilis
• Proteus sp (indole positive)
• Serratia marcescens
• Salmonella sp
• Shigella sp
• Providencia sp
• Citrobacter freundii
• Listeria monocytogenes
ureus (both penicillin-
resistant and penicillin-sensitive)

The aminoglycoside antibiotics in general have limited
activity against gram-positive pathogens, although Staphylococcus aureus and Listeria monocytogenes
are susceptible to amikacin as noted above.

Amikacin has been shown to be effective against

many aminoglycoside-resistant strains due to its

ability to resist degradation by aminoglycoside

inactivating enzymes known to affect gentamicin,

tobramycin and kanamycin^2.

CLINICAL PHARMACOLOGY

Endometrial Tissue Concentrations
Comparisons of amikacin activity in endometrial biopsy tissue following intrauterine infusion with
that following intramuscular injection of AMIGLYDE-V in mares demonstrate superior endometrial
tissue concentrations when the drug is administered by
the intrauterine route.
Intrauterine infusion of 2 grams AMIGLYDE-V daily for three consecutive days in mares results in
peak concentrations typically exceeding 40 mcg/g of endometrial biopsy tissue within one hour after
infusion. Twenty-four hours after each treatment amikacin activity is still detectable at
concentrations averaging 2 to 4 mcg/g. However, the drug is not appreciably absorbed systemically
following intrauterine infusion. Endometrial tissue concentrations following intramuscular
injection are roughly parallel, but are typically somewhat lower
than corresponding serum concentrations of amikacin.

SAFETY

AMIGLYDE-V is non-irritating to equine endometrial
tissue when infused into the uterus as directed (see ADMINISTRATION AND DOSAGE). In laboratory
animals as well as equine studies, the drug was generally found not to be irritating when injected
intravenously, subcutaneously or intramuscularly.
Although amikacin, like other aminoglycosides, is potentially nephrotoxic, ototoxic and neurotoxic,
parenteral (intravenous) administration of AMIGLYDE-V (amikacin sulfate injection) twice daily at
dosages of up to 10 mg/lb for 15 consecutive days in horses resulted in no clinical, laboratory or
histopathologic evidence of toxicity.
Intrauterine infusion of 2 grams of AMIGLYDE-V
8 hours prior to breeding by natural service did not impair fertility in mares. Therefore, mares
should not be bred for at least 8 hours following uterine infusion.

INDICATIONS

AMIGLYDE-V is indicated for the treatment of uterine
infections (endometritis, metritis and pyometra) in mares, when caused by susceptible organisms
including Escherichia coli, Pseudomonas sp and Klebsiella sp. The use of AMIGLYDE-V in eliminating
infections caused by the above organisms has been shown clinically to improve fertility in infected
mares.
While nearly all strains of Escherichia coli,
Pseudomonas sp and Klebsiella sp, including those that are resistant to gentamicin, kanamycin or other
aminoglycosides, are susceptible to amikacin at levels achieved following treatment, it is
recommended that the invading organism be cultured and its susceptibility demonstrated as a guide
to therapy. Amikacin susceptibility discs, 30 mcg, should be used for determining in vitro susceptibility.

ADMINISTRATION AND DOSAGE

For treatment of uterine infections in mares, 2 grams
(8 mL) of AMIGLYDE-V, mixed with 200 mL 0.9% Sodium chloride injection, USP and aseptically infused
into the uterus daily for three consecutive days, has been found to be the most efficacious dosage.

CONTRAINDICATIONS

There are no known contraindications for the use of
AMIGLYDE-V in horses other than a history of hypersensitivity to amikacin.

PRECAUTIONS

Although AMIGLYDE-V is not absorbed to an appreciable
extent following intrauterine infusion, concurrent use of other aminoglycosides should
be avoided because of the potential for additive effects.

.

ADVERSE REACTIONS

No adverse reactions or other side effects have been reported.

WARNINGS

Do not use in horses intended for human consumption.

In vitro studies have demonstrated that when sperm are exposed to the preservative which is present in the 48 mL

vials (250 mg/mL) sperm viability is impaired.

HOW SUPPLIED

AMIGLYDE-V (amikacin sulfate injection) Veterinary

Solution is supplied as a colorless solution which is stable

when stored at or below 25°C (77°F). Use contents within

3 months of first vial puncture.

48 mL vial, 250 mg/mL

Store at or below 25°C (77°F).

REFERENCES

1. Price, K.E., et al: Microbiological Evaluation of BB-K8, a New Semisynthetic Aminoglycoside. J Antibiot 25: 709–731, 1972.

2. Davies, J., Courvalin, P.: Mechanisms of Resistance to Aminoglycosides. Am J Med 62: 868–872, 1977.

Approved by FDA under NADA # 127-892
zoetis
Manufactured and Distributed by:
Zoetis Inc.
Kalamazoo, MI 49007

Revised: July 2019

40028299